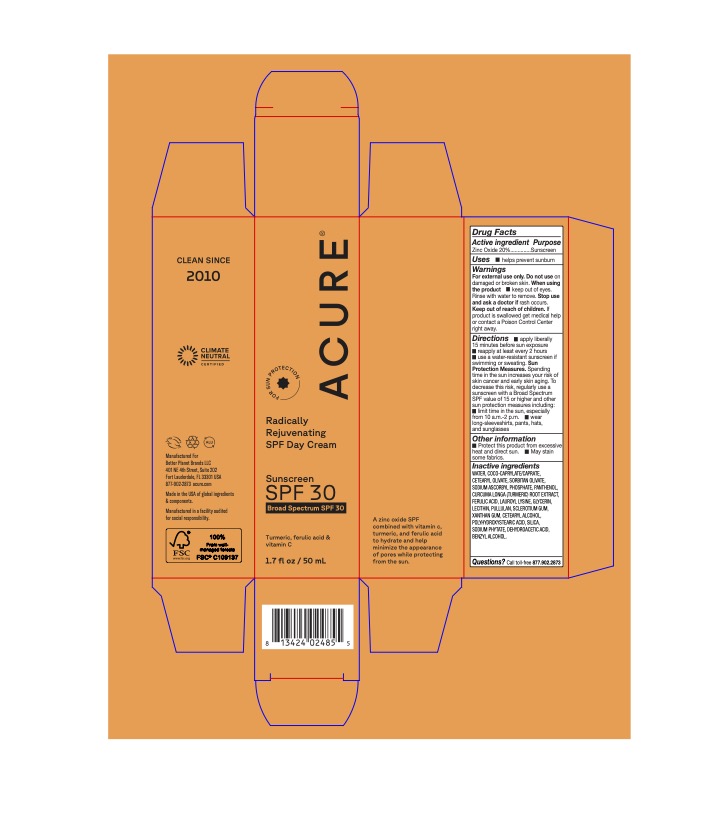 DRUG LABEL: Radically Rejuvenating SPF Day Cream
NDC: 54136-152 | Form: CREAM
Manufacturer: Better Planet Brands LLC
Category: otc | Type: HUMAN OTC DRUG LABEL
Date: 20251203

ACTIVE INGREDIENTS: ZINC OXIDE 20 g/100 g
INACTIVE INGREDIENTS: SILICON DIOXIDE; WATER; BENZYL ALCOHOL; COCO-CAPRYLATE/CAPRATE; GLYCERIN; SORBITAN OLIVATE; PULLULAN; CETEARYL OLIVATE; TURMERIC; PANTHENOL; FERULIC ACID; SODIUM ASCORBYL PHOSPHATE; DEHYDROACETIC ACID; LECITHIN, SOYBEAN; HEXASODIUM PHYTATE; BETASIZOFIRAN; POLYHYDROXYSTEARIC ACID (2300 MW); XANTHAN GUM; LAUROYL LYSINE; CETOSTEARYL ALCOHOL

Radically Rejuvenating SPF Day Cream

Active ingredients

Zinc Oxide 20%

Purpose

Sunscreen

Uses

• helps prevent sunburn

Warnings

For external use only.

Do not use on damaged or broken skin.

WHEN USING

When using the product • keep out of eyes. Rinse with water to remove.

Stop use and ask a doctor if rash occurs.

Keep out of reach of children. If product is swallowed get medical help or contact a Poison Control Center right away.

Directions

• apply liberally 15 minutes before sun exposure reapply at least every 2 hours use a water-resistant sunscreen if swimming or sweating. Sun Protection Measures. Spending time in the sun increases your risk of skin cancer and early skin aging. To decrease this risk, regularly use a sunscreen with a Broad Spectrum SPF value of 15 or higher and other sun protection measures including:

• limit time in the sun, especially from 10 a.m.-2 p.m.

• wear long-sleeveshirts, pants, hats, and sunglasses

Other information

• Protect this product from excessive heat and direct sun. • May stain some fabrics.

Inactive Ingredients

WATER, COCO-CAPRYLATE/CAPRATE, CETEARYL OLIVATE, SORBITAN OLIVATE, SODIUM ASCORBYL PHOSPHATE, PANTHENOL, CURCUMA LONGA (TURMERIC) ROOT EXTRACT, FERULIC ACID, LAUROYL LYSINE, GLYCERIN, LECITHIN, PULLULAN, SCLEROTIUM GUM, XANTHAN GUM, CETEARYL ALCOHOL, POLYHYDROXYSTEARIC ACID, SILICA, SODIUM PHYTATE, DEHYDROACETIC ACID, BENZYL ALCOHOL

Questions?

Call toll-free 877.902.2873